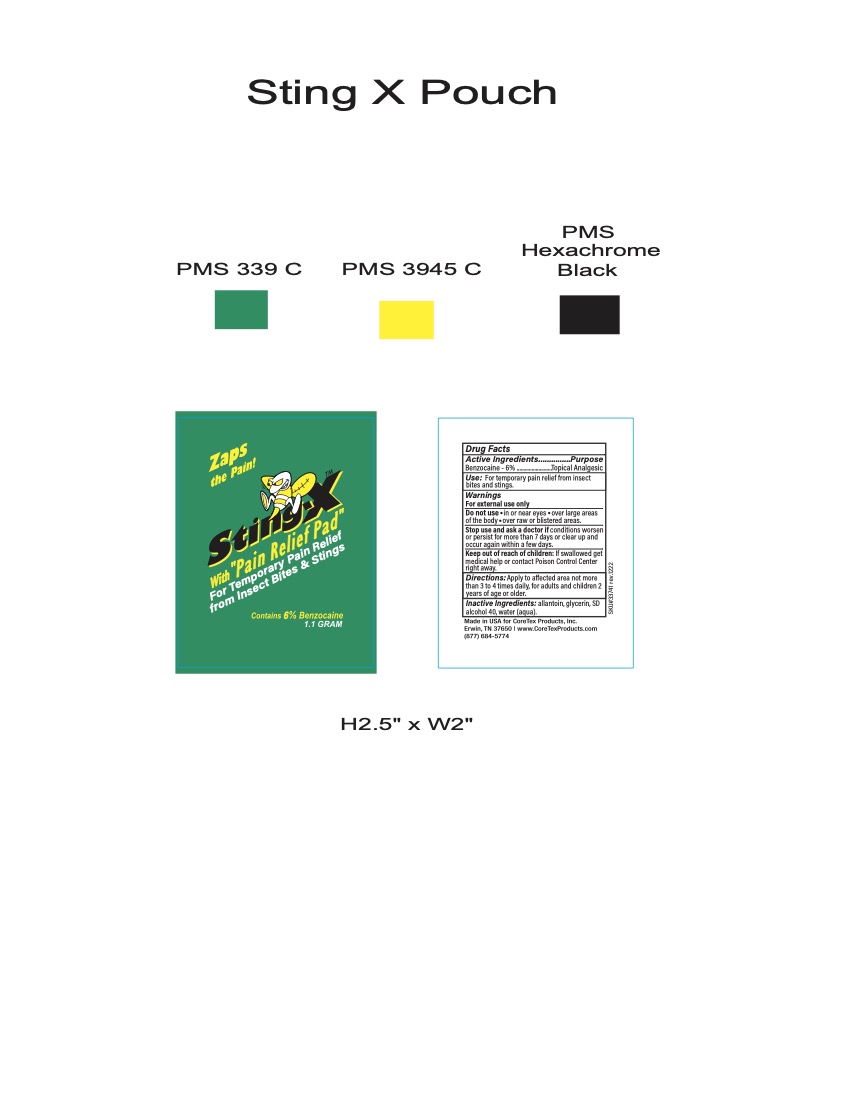 DRUG LABEL: StingX
NDC: 65753-350 | Form: SWAB
Manufacturer: CoreTex Products Inc
Category: otc | Type: HUMAN OTC DRUG LABEL
Date: 20231022

ACTIVE INGREDIENTS: BENZOCAINE 6 g/100 mL
INACTIVE INGREDIENTS: ALCOHOL; WATER; ALLANTOIN; GLYCERIN

Cortex StingX
65753-350

Active Ingredients

Benzocaine 6%

Purpose

Topical Analgesic

Use

For temporary pain relief from insect bites and stings

Warnings

For external use only

Do Not Use

- in or near eyes
- over large areas of the body
- over raw or blistered areas

Stop use and aska doctor if

- conditions worsen or persist for more than 7 days or clear up and occur again within a few days

Keep out of reach of children

If swallowed get medical help or contact Poison Control center right away.

Directions

Apply to affected area not more than 3 to 4 times daily, for adults and children 2 years of age or older.

Inactive Ingredients

allantoin, glycerin, SD alcohol 40, water (aqua)

OTHER SAFETY INFORMATION

Made in USA for CoreTex Products, Inc.

Erwin, TN 37650 / www.CoreTexProducts.com

(877)684-5774